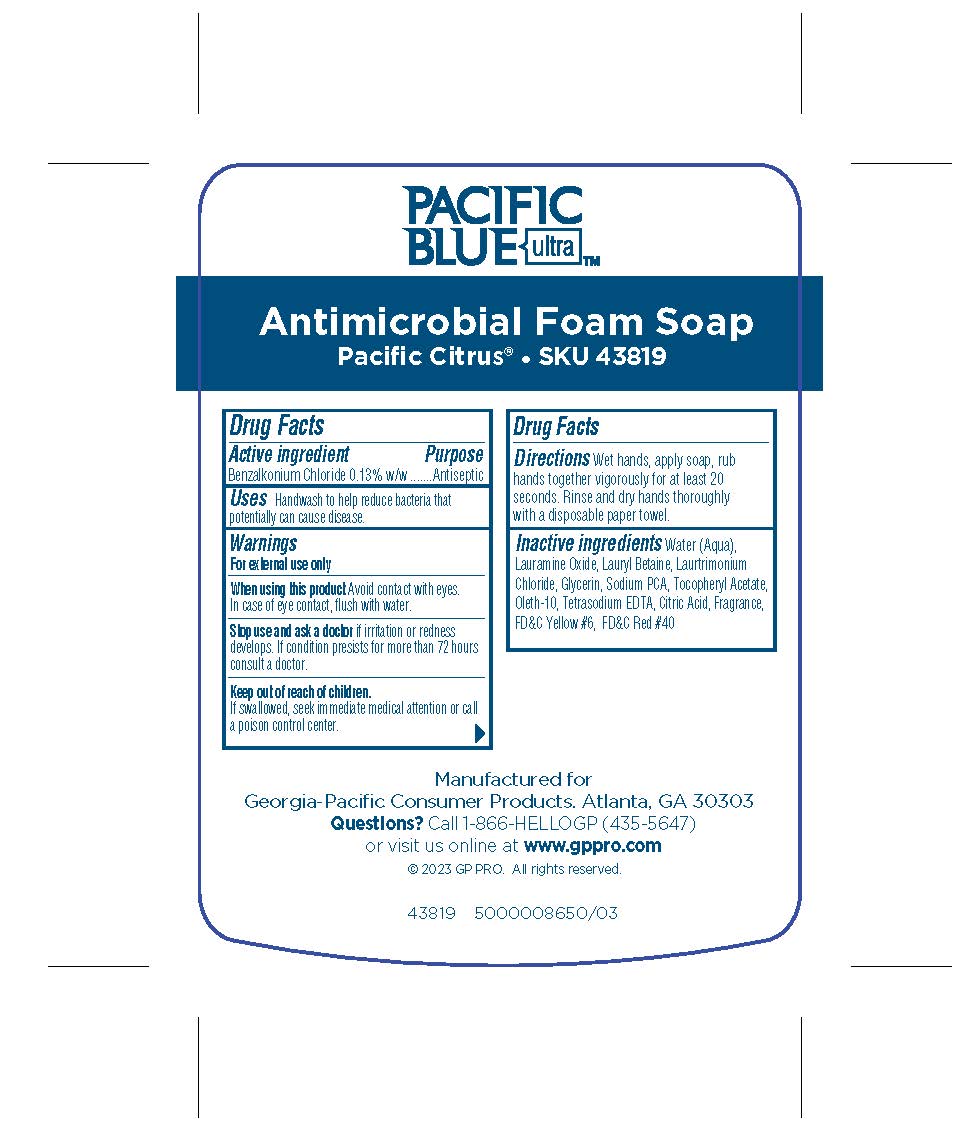 DRUG LABEL: Pacific Blue ultra Antimicrobial Foam Pacific Citrus
NDC: 54622-317 | Form: SOLUTION
Manufacturer: Georgia-Pacific Consumer Products
Category: otc | Type: HUMAN OTC DRUG LABEL
Date: 20240502

ACTIVE INGREDIENTS: BENZALKONIUM CHLORIDE 0.13 g/100 mL
INACTIVE INGREDIENTS: FD&C RED NO. 40; WATER; .ALPHA.-TOCOPHEROL, DL-; EDETATE SODIUM; SODIUM PIDOLATE; OLETH-10; FD&C YELLOW NO. 6; GLYCERIN; LAURTRIMONIUM CHLORIDE; ANHYDROUS CITRIC ACID; LAURYL BETAINE; LAURAMINE OXIDE

54622-317

Drug Facts

Active ingredient

Benzalkonium chloride, 0.13% w/w

Purpose

Antiseptic

Use

Handwash to help reduce bacteria that potentially can cause disease.

Warnings

- For external use only

When using this product

Avoid contact with eyes. In case of eye contact, flush with water.

Stop use

if irritation or redness develops. If condition persists for more than 72 hours consult a doctor.

Keep out of reach of children.

If swallowed, seek immediate medical attention or call a poison control center.

Directions

Wet hands, apply soap, rub hands together vigorously for at least 20 seconds.

Rinse and dry hands thoroughly with a disposable paper towel.

Inactive ingredients

Water (Aqua), Lauramine Oxide, Lauryl Betaine, Laurtrimonium
Chloride, Glycerin, Sodium PCA, Tocopheryl Acetate,
Oleth-10, Tetrasodium EDTA, Citric Acid, Fragrance,
FD&C Yellow #6, FD&C Red #40